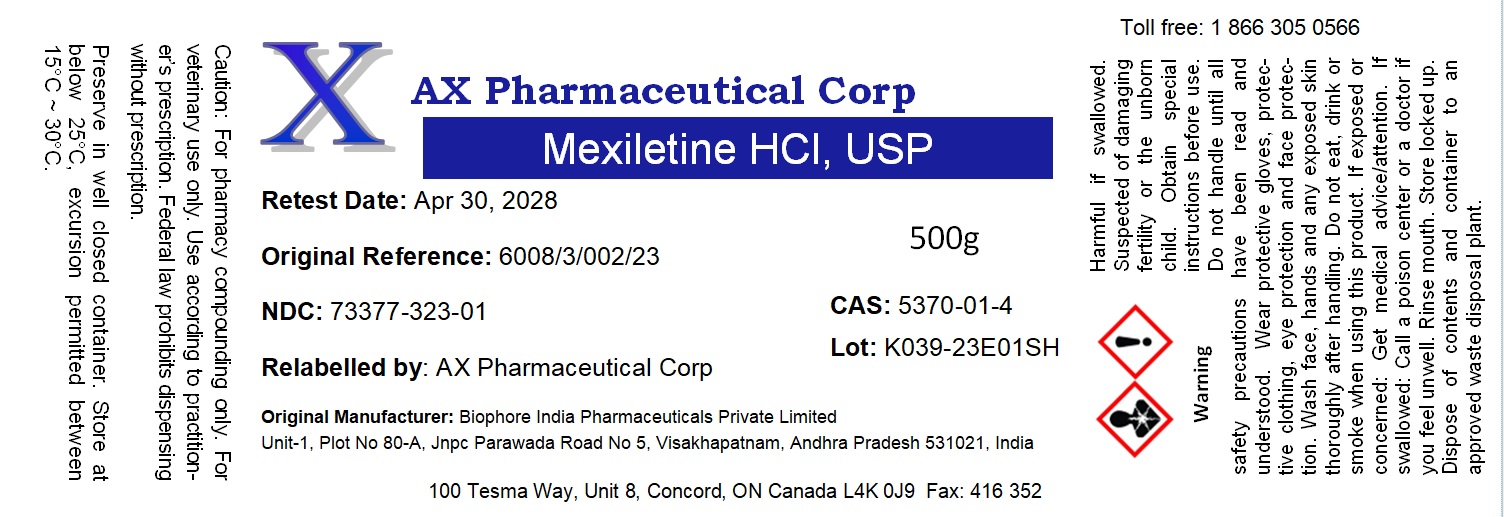 DRUG LABEL: Mexiletine HCl
NDC: 73377-323 | Form: POWDER
Manufacturer: AX Pharmaceutical Corp
Category: other | Type: BULK INGREDIENT - ANIMAL DRUG
Date: 20250512

ACTIVE INGREDIENTS: MEXILETINE HYDROCHLORIDE 1 g/1 g

Mexiletine HCl